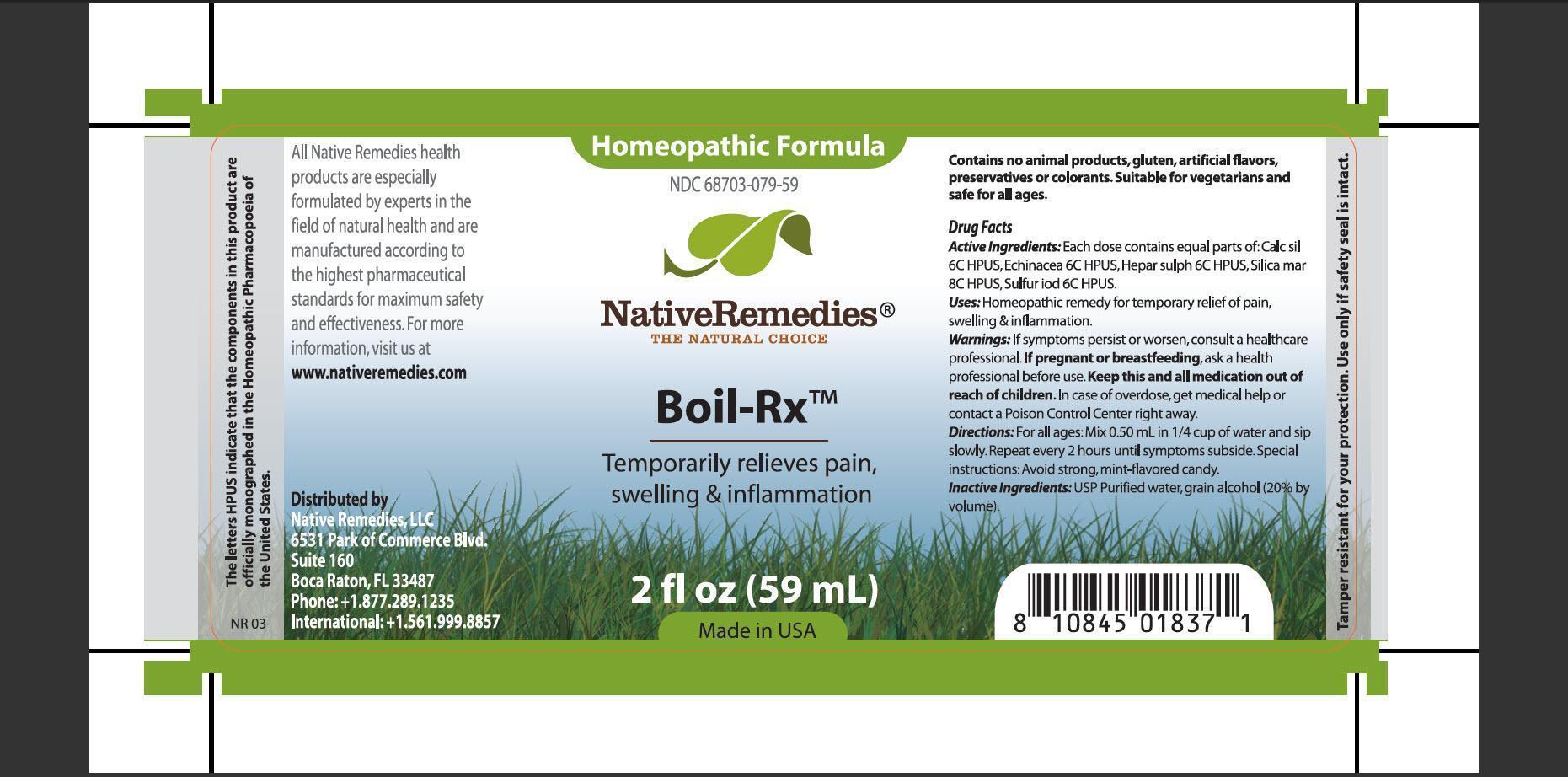 DRUG LABEL: Boil-Rx
                
NDC: 68703-079 | Form: TINCTURE
Manufacturer: Native Remedies, LLC
Category: homeopathic | Type: HUMAN OTC DRUG LABEL
Date: 20130430

ACTIVE INGREDIENTS: CALCIUM SILICATE 6 [hp_C]/1 mL; ECHINACEA, UNSPECIFIED 6 [hp_C]/1 mL; CALCIUM SULFIDE 6 [hp_C]/1 mL; SILICON DIOXIDE 8 [hp_C]/1 mL; SULFUR IODIDE 6 [hp_C]/1 mL
INACTIVE INGREDIENTS: WATER; ALCOHOL

Boil-Rx

PURPOSE

Temporarily relieves pain, swelling and inflammation

ACTIVE INGREDIENT

Active Ingredients: Each dose contains equal parts of: Calc sil 6C HPUS, Echinacea 6C HPUS, Hepar sulph 6C HPUS, Silica mar 8C HPUS, Sulfur iod 6C HPUS

INDICATIONS AND USAGE

Uses: Homeopathic remedy for temporarily relief of pain, swelling and inflammation

WARNINGS

Warnings: If symptoms persist or worsen, consult a healthcare professional

PREGNANCY OR BREAST FEEDING

If pregnant or breastfeeding, ask a health professional before use

KEEP OUT OF REACH OF CHILDREN

Keep this and all medication out of reach of children

OVERDOSAGE

In case of overdose, get medical help or contact a Poison Control Center right away

DOSAGE AND ADMINISTRATION

Directions: For all ages: Mix 0.50 mL in 1/4 cup of water and sip slowly. Repeat every 2 hours until symptoms subside. Special instructions: Avoid strong, mint-flavored candy

INACTIVE INGREDIENT

Inactive Ingredients: USP Purified water, grain alcohol (20% by volume)

PATIENT COUNSELING INFORMATION

The letters HPUS indicate that the component in this product are officially monographed in the Homeopathic Pharmacopoeia of the United States

All Native Remedies health product are especially formulated by expert in the field of natural health and are manufactured according to the highest pharmaceutical standards for maximum safety and effectiveness. For more information, visit us at www.nativeremedies.com

Distributed by
Native Remedies, LLC
6531 Park of Commerce Blvd.
Suite 160
Boca Raton, FL 33487
Phone:+1.877.289.1235
International: +1.561.999.8857

Contains no animal products, gluten, artificial flavors, preservatives or colorants. Suitable for vegetarians and safe for all ages

STORAGE AND HANDLING

Tamper resistant for you protection. Use only if safety seal is intact